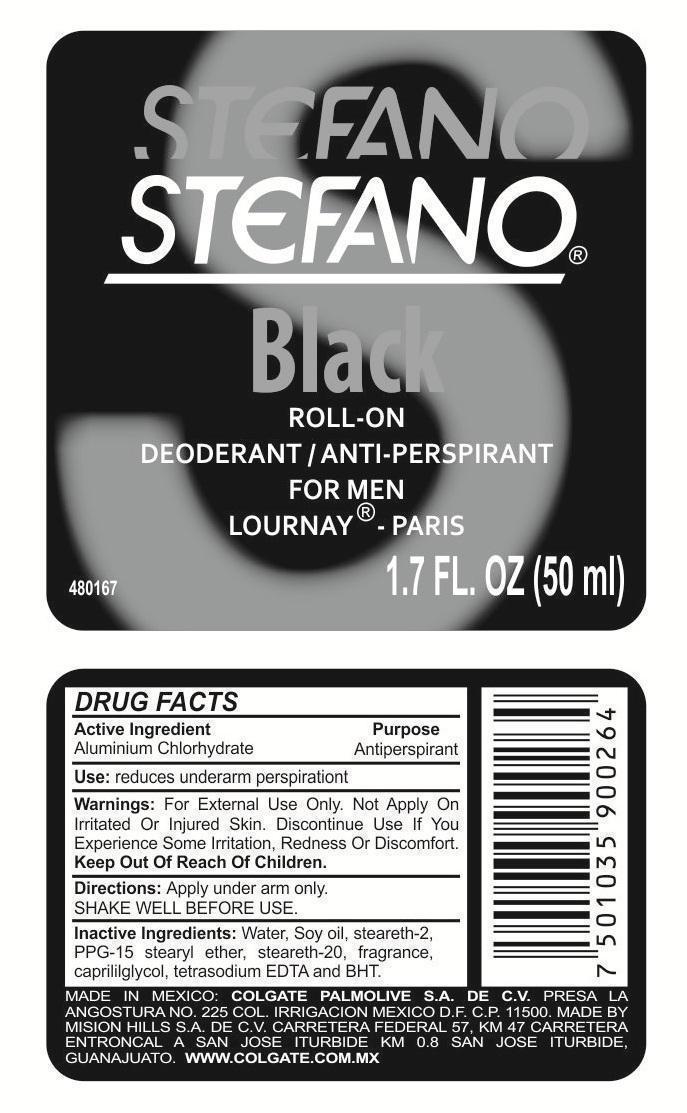 DRUG LABEL: Stefano
NDC: 69670-900 | Form: STICK
Manufacturer: Impulsora Sahuayo, S.A. de C.V
Category: otc | Type: HUMAN OTC DRUG LABEL
Date: 20201219

ACTIVE INGREDIENTS: ALUMINUM CHLOROHYDRATE 25 g/100 mL
INACTIVE INGREDIENTS: WATER; PPG-15 STEARYL ETHER; STEARETH-20; CAPRYLYL GLYCOL; STEARETH-2; BUTYLATED HYDROXYTOLUENE; EDETATE SODIUM

Stefano Black Roll-On

ACTIVE INGREDIENT:

ALUMINUM CHLOROHYDRATE

PURPOSE

Antitraspirant

KEEP OUT OF THE REACH OF CHILDREN

WARNINGS:

For external use only. Do not apply on irritated or injured skin. Discontinue use if you experience some irritation, redness or discomfort.

Directions:

Apply under arm only.

SHAKE WELL BEFORE USE.

INACTIVE INGREDIENT

Water, soy oil, stearth-2, PPG-15 stearyl ether, steareth-20, fragance, caprylyl glycol, tetrasodium edta, and bht

INDICATIONS AND USAGE

SHAKE WELL BEFORE USE

Apply under arm only